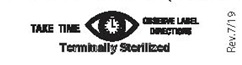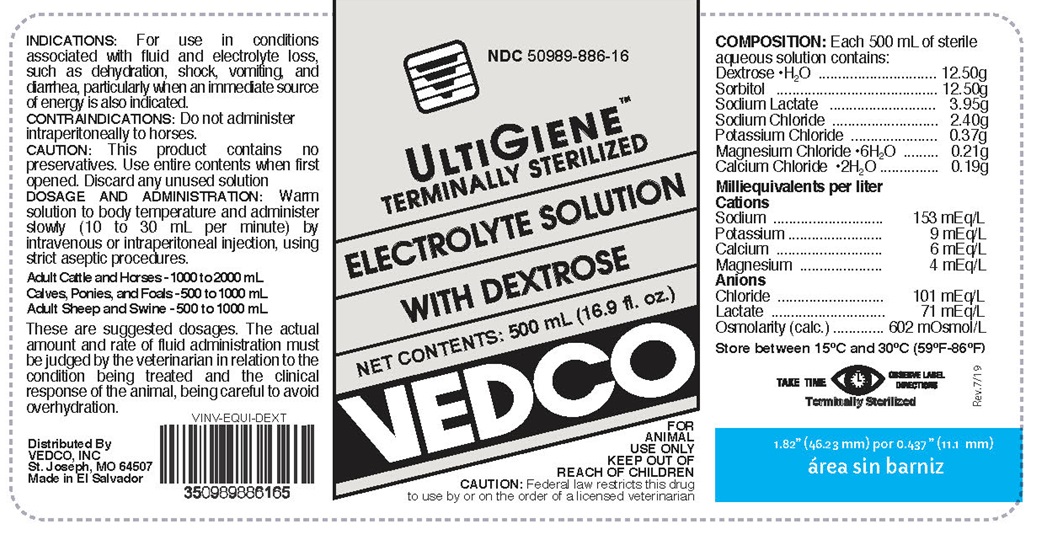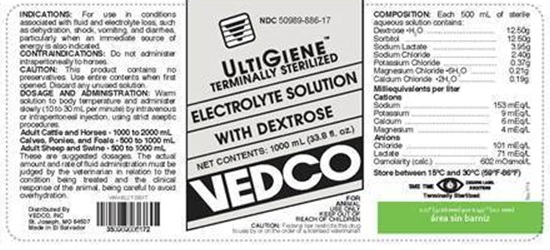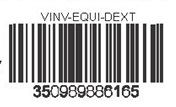 DRUG LABEL: Ultigene
NDC: 50989-886 | Form: INJECTION, SOLUTION
Manufacturer: Vedco
Category: animal | Type: PRESCRIPTION ANIMAL DRUG LABEL
Date: 20190809

ACTIVE INGREDIENTS: Dextrose Monohydrate 12.50 g/500 mL; Sorbitol 12.50 g/500 mL; Sodium Lactate 3.95 g/500 mL; Sodium Chloride 2.40 g/500 mL; Potassium Chloride 0.37 g/500 mL; Magnesium Chloride 0.21 g/500 mL; Calcium Chloride 0.19 g/500 mL

ELECTROLYTE SOLUTION WITH DEXTROSE

Composition

Each 500 mL of sterile aqueous solution contains:

Dextrose.H2O 12.50g

Sorbitol 12.50g

Sodium Lactate 3.95g

Sodium Chloride 2.40g

Potassium Chloride 0.37g

Magnesium Chloride.6H2O 0.21g

Calcium Chloride.2H2O 0.19g

Milliequivalents per liter

Cations

Sodium 153mEq/L

Potassium 9mEq/L

Calcium 6mEq/L

Magnesium 4mEq/L

Anions

Chloride 101 mEq/L

Lactate 71 mEq/L

Osmolarity (calc.) 602 mOsmol/L

Indications

For use in conditions associated with fluid and electrolyte loss such as dehydration, shock, vomitting, and diarrhea, particularly when an immediate source of energy is also indicated

Contradictions

Do not administer intraperitoneally to horses

Dosage and Administration

This product contains no preservatives. Use entire contents when first opened. Discard any unused solution.

Warm solution to body temperature and administer slowly (10 to 30 mL per minute) by intravenous or intraperitoneal injections, using strict aseptic procedures.

Adult Cattles and Horses - 1000 to 2000 mL

Calves, Ponies, and Foals - 500 to 1000 mL

Adult, Sheep and Swine - 500 to 1000 mL

These are suggested dosages. The actual amount and rate of fluid administration must be judged by the veterinarian in relation to the condition being treated and the clinical response of the animal, being careful to avoid overhydration

VETERINARY INDICATIONS

FOR ANIMAL USE ONLY

Warning

KEEP OUT OF REACH OF CHILDREN

CAUTION:

Federal law restricts this drug to use by or on the order of a licensed veterinarian

Storage

Store between 15oC and 30oC (59oF - 86oF)

Distributed By:

VEDCO INC

St. Joseph, MO, 64507

Made in El Salvador

Principal Display Panel

NDC 50989-886-16

ULTIGIENETM TERMINALLY STERILIZED

ELECTROLYTE SOLUTION WITH DEXTROSE

NET CONTENTS: 500 mL (16.9 fl. oz.)

VEDCO

NDC 50989-886-17

ULTIGIENETM TERMINALLY STERILIZED

ELECTROLYTE SOLUTION WITH DEXTROSE

NET CONTENTS: 1000 mL (33.8 fl. oz.)

VEDCO